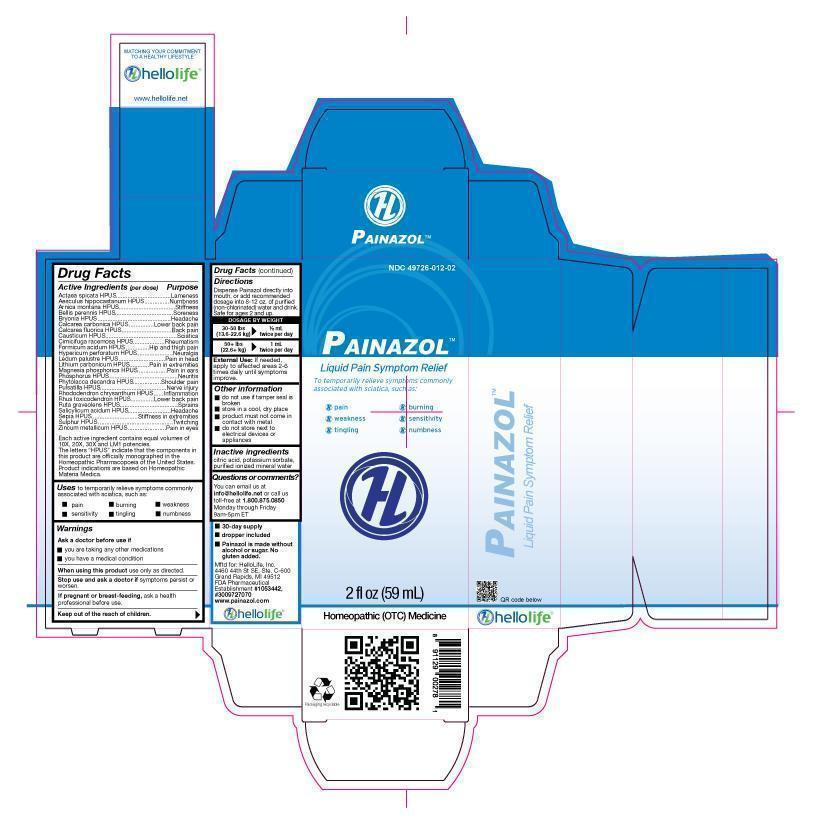 DRUG LABEL: Painazol
NDC: 49726-012 | Form: LIQUID
Manufacturer: Hello Life, Inc.
Category: homeopathic | Type: HUMAN OTC DRUG LABEL
Date: 20181226

ACTIVE INGREDIENTS: ACTAEA SPICATA ROOT 10 [hp_X]/59 mL; AESCULUS HIPPOCASTANUM FLOWER 10 [hp_X]/59 mL; ARNICA MONTANA 10 [hp_X]/59 mL; BELLIS PERENNIS 10 [hp_X]/59 mL; BRYONIA ALBA ROOT 10 [hp_X]/59 mL; OYSTER SHELL CALCIUM CARBONATE, CRUDE 10 [hp_X]/59 mL; CALCIUM FLUORIDE 10 [hp_X]/59 mL; CAUSTICUM 10 [hp_X]/59 mL; BLACK COHOSH 10 [hp_X]/59 mL; FORMIC ACID 10 [hp_X]/59 mL; HYPERICUM PERFORATUM 10 [hp_X]/59 mL; LEDUM PALUSTRE TWIG 10 [hp_X]/59 mL; LITHIUM CARBONATE 10 [hp_X]/59 mL; MAGNESIUM PHOSPHATE, DIBASIC TRIHYDRATE 10 [hp_X]/59 mL; PHOSPHORUS 10 [hp_X]/59 mL; PHYTOLACCA AMERICANA ROOT 10 [hp_X]/59 mL; PULSATILLA VULGARIS 10 [hp_X]/59 mL; RHODODENDRON AUREUM LEAF 10 [hp_X]/59 mL; TOXICODENDRON PUBESCENS LEAF 10 [hp_X]/59 mL; RUTA GRAVEOLENS FLOWERING TOP 10 [hp_X]/59 mL; SALICYLIC ACID 10 [hp_X]/59 mL; SEPIA OFFICINALIS JUICE 10 [hp_X]/59 mL; SULFUR 10 [hp_X]/59 mL; ZINC 10 [hp_X]/59 mL
INACTIVE INGREDIENTS: POTASSIUM SORBATE; WATER; CITRIC ACID MONOHYDRATE

Drug Facts

Active Ingredient (per dose)

Actaea spicata HPUS, Aesculus hippocastanum HPUS, Arnica Montana HPUS, Bellis perennis HPUS, Bryonia HPUS, Calcarea carbonica HPUS, Calcarea fluorica HPUS, Causticum HPUS, Cimicifuga racemosa HPUS, Formicum acidum HPUS, Hypericum perforatum HPUS, Ledum palustre HPUS, Lithium carbonicum HPUS, Magnesia phosphorica HPUS, Phosphorus HPUS, Phytolacca decandra HPUS, Pulsatilla HPUS, Rhododendron chrysanthum HPUS, Rhus toxicodendron HPUS, Ruta graveolens HPUS, Salicylicum acidum HPUS, Sepia HPUS, Sulphur HPUS, Zincum metallicum HPUS
Each active ingredient contains equal volumes of 10X, 20X, 30X and LM1 potencies. The letters "HPUS" indicate that the components in this product are officially monographed in the Homeopathic Pharmacopoeia of the United States. Product indications are based on Homeopathic Materia Medica.

Purpose

Actaea spicata HPUS.......................................................Lameness

Aesculus hippocastanum HPUS........................................Numbness

Arnica Montana HPUS......................................................Stiffness

Bellis perennis HPUS.......................................................Soreness

Bryonia HPUS.................................................................Headache

Calcarea carbonica HPUS................................................Lower back pain

Calcarea fluorica HPUS....................................................Back pain

Causticum HPUS............................................................Sciatica

Cimicifuga racemosa HPUS.............................................Rheumatism

Formicum acidum HPUS..................................................Hip and thigh pain

Hypericum perforatum HPUS............................................Neuralgia

Ledum palustre HPUS......................................................Pain in head

Lithium carbonicum HPUS................................................Pain in extremities

Magnesia phosphorica HPUS...........................................Pain in ears

Phosphorus HPUS...........................................................Neuritis

Phytolacca decandra HPUS..............................................Shoulder pain

Pulsatilla HPUS...............................................................Nerve injury

Rhododendron chrysanthum HPUS....................................Inflammation

Rhus toxicodendron HPUS................................................Lower back pain

Ruta graveolens HPUS.....................................................Sprains

Salicylicum acidum HPUS................................................Headaches

Sepia HPUS....................................................................Stiffness in extremities

Sulphur HPUS..................................................................Twitching

Zincum metallicum HPUS..................................................Pain in eyes

Uses

For temporary relief of symptoms commonly associated with sciatica, such as:

- pain
- sensitivity
- burning
- tingling
- weakness
- numbness

Warnings

Ask a doctor before use if

- you are taking any other medications
- you have a medical condition

When using this product, use only as directed.

Stop use and ask a doctor if symptoms persist or worsen.

PREGNANCY OR BREAST FEEDING

If pregnant or breast-feeding, ask a health professional before use.

Keep out of the reach of children.

Directions

Dispense Painazol directly into mouth, or add recommended dosage to 8-12 oz purified (non-chlorinated water) and drink.

Dosage by Weight:

30-50 lbs (13.6-22.6 kg) 1/2 mL twice per day

50+ lbs (22.6+ kg) 1 mL twice per day.

External Use: If needed, apply to affected areas 2-6 times daily until symptoms improve.

Other Information

- do not use if tamper seal is broken
- store in a cool, dry place
- product must not come in contact with metal
- do not store next to electrical devices or appliances

Inactive ingredients

citric acid, potassium sorbate, purified ionized mineral water

Questions or comments

You can email us at info@hellolife.net or give us a call toll-free at 1.800.875.0850 Monday through Friday 9am-5pm ET

DESCRIPTION

- 30-day supply
- dropper included
- Painazol is made without alcohol or sugar. No gluten added.

Mftd for: HelloLife, Inc. 4460 44th St. SE Ste. C-600 Grand Rapids, MI 49512 FDA Pharmaceutical Establishment #1053442, #3009727070 www.painazol.com

PACKAGE LABEL

NDC 49726-012-02

PAINAZOLTM

Liquid Pain Symptom Relief

For temporary relief of symptoms commonly associated with sciatica, such as:

- pain
- weakness
- tingling
- burning
- sensitivity
- numbness

2 FL OZ (59 mL)
Homeopathic (OTC) Medicine